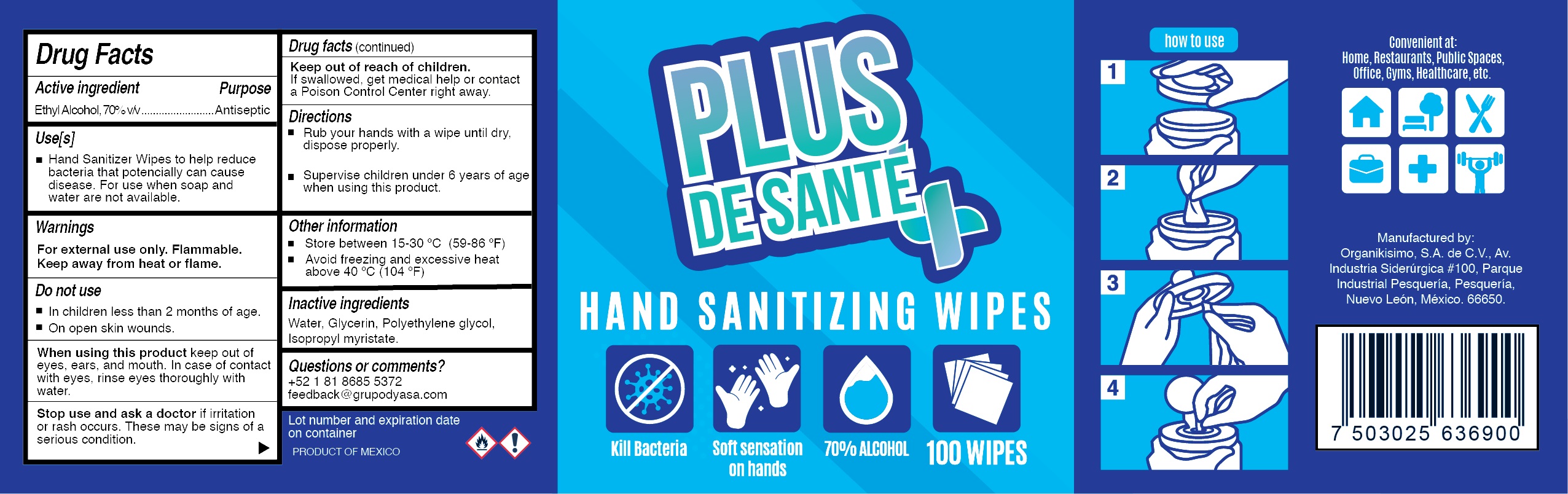 DRUG LABEL: Hand Sanitizer wipes
NDC: 79337-158 | Form: CLOTH
Manufacturer: ORGANIKISIMO SA DE CV
Category: otc | Type: HUMAN OTC DRUG LABEL
Date: 20201202

ACTIVE INGREDIENTS: ALCOHOL 70 mL/100 mL
INACTIVE INGREDIENTS: POLYETHYLENE GLYCOL, UNSPECIFIED 0.37 mL/100 mL; GLYCERIN 0.68 mL/100 mL; WATER 28.46 mL/100 mL; ISOPROPYL MYRISTATE 0.49 mL/100 mL

HAND SANITIZER WIPES BOTTLE

Active Ingredient(s)

Alcohol 70% v/v. Purpose: Antiseptic

Purpose

Antiseptic, Hand Sanitizer wipes

Use

Hand Sanitizer wipes to help reduce bacteria that potentially can cause disease. For use when soap and water are not available.

Warnings

For external use only. Flammable. Keep away from heat or flame

Do not use

- in children less than 2 months of age
- on open skin wounds

When using this product keep out of eyes, ears, and mouth. In case of contact with eyes, rinse eyes thoroughly with water.
Stop use and ask a doctor if irritation or rash occurs. These may be signs of a serious condition.
Keep out of reach of children. If swallowed, get medical help or contact a Poison Control Center right away.

Stop use and ask a doctor if irritation or rash occurs. These may be signs of a serious condition.

Keep out of reach of children. If swallowed, get medical help or contact a Poison Control Center right away.

Directions

- . Rub hands together until dry. disponse properly.
- Supervise children under 6 years of age when using this product.

Other information

- Store between 15-30C (59-86F)
- Avoid freezing and excessive heat above 40C (104F)

Inactive ingredients

water,Glycerin, Polyethylene glycol, Isopropyl myristate

Package Label - Principal Display Panel

210 ML NDC 79337-158-01